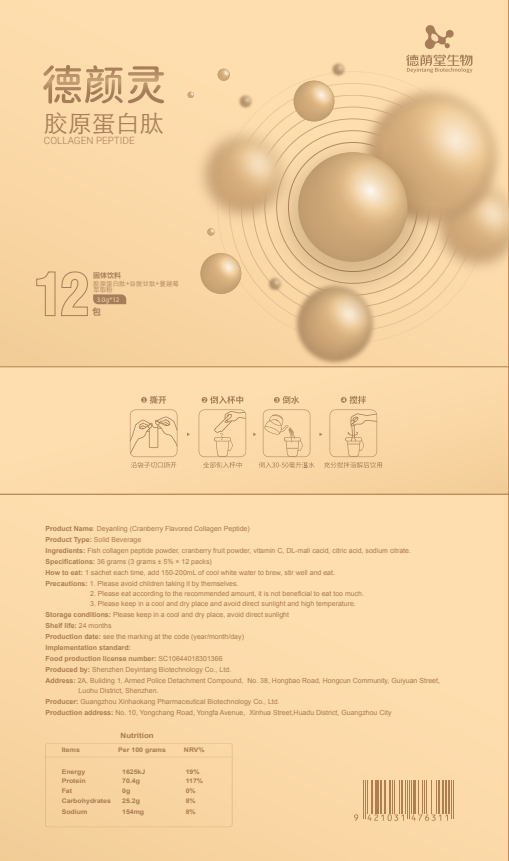 DRUG LABEL: Deyanling(Cranberry Flavored Collagen Peptide)
NDC: 82570-004 | Form: POWDER
Manufacturer: Shenzhen Deyintang Biotechnology Co., Ltd.
Category: otc | Type: HUMAN OTC DRUG LABEL
Date: 20220221

ACTIVE INGREDIENTS: COLLAGEN, SOLUBLE, FISH SKIN 80 g/100 g; GLUTATHIONE 5 g/100 g; ASCORBIC ACID 2 g/100 g
INACTIVE INGREDIENTS: CITRIC ACID MONOHYDRATE; CRANBERRY; SODIUM CITRATE; MALIC ACID

ACTIVE INGREDIENT

Fish collagen peptide powder

vitamin C

Glutathione

INACTIVE INGREDIENT

cranberry fruit powder, DL-mali cacid, citric acid, sodium citrate

PURPOSE

health care

Please avoid children taking it by themselves.

How to eat

1 sachet each time, add 150-200mL of cool white water to brew, stir well and eat.

INDICATIONS AND USAGE

Please eat according to the recommended amount, it is not beneficial to eat too much.

Storage conditions

Please keep in a cool and dry place, avoid direct sunlight

WARNINGS

1.Please avoid children taking it by themselves.
2.Please eat according to the recommended amount, it is not beneficial to eat too much.
3.Please keep in a cool and dry place and avoid direct sunlight and high temperature.